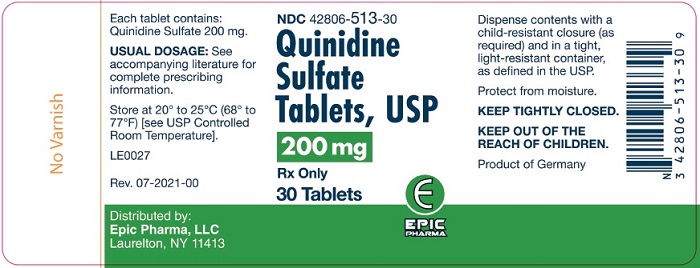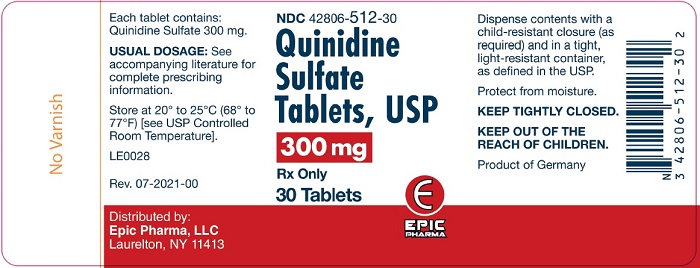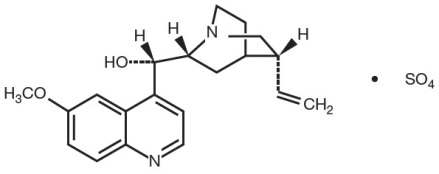 DRUG LABEL: QUINIDINE SULFATE
NDC: 42806-513 | Form: TABLET
Manufacturer: EPIC PHARMA, LLC
Category: prescription | Type: HUMAN PRESCRIPTION DRUG LABEL
Date: 20231108

ACTIVE INGREDIENTS: QUINIDINE SULFATE 200 mg/1 1
INACTIVE INGREDIENTS: SUCROSE; STARCH, CORN; MICROCRYSTALLINE CELLULOSE; ZINC STEARATE

Quinidine Sulfate Tablets, USP

DESCRIPTION

Quinidine is an antimalarial schizonticide and an antiarrhythmic agent with class 1A activity; it is the d-isomer of quinine, and its molecular weight is 324.43. Quinidine sulfate is the sulfate salt of quinidine; its chemical name is cinchonan-9-ol, 6’- methoxy-, (9S)-, sulfate (2:1) dihydrate; its structural formula is:

Its molecular formula is: C40H48N4O4∙H2SO4∙2H2O; and its molecular weight is 782.96, of which 82.9% is quinidine base.

Quinidine sulfate occurs as fine needle-like, white crystals, frequently cohering in masses, or fine, white powder. It is odorless, has a very bitter taste, and darkens on exposure to light. It is slightly soluble in water, soluble in alcohol and in chloroform, and insoluble in ether.

Each tablet, for oral administration, contains 200 mg of quinidine sulfate (equivalent to 166 mg of quinidine base) 300 mg of quinidine sulfate (equivalent to 249 mg of quinidine base). In addition, each tablet contains the following inactive ingredients: confectioner’s sugar, corn starch, microcrystalline cellulose, pregelatinized starch and zinc stearate.

CLINICAL PHARMACOLOGY

Pharmacokinetics and Metabolism

The absolute bioavailability of quinidine from quinidine sulfate tablets is about 70%, but this varies widely (45 to 100%) between patients. The less-than-complete bioavailability is the result of first-pass metabolism in the liver. Peak serum levels generally appear about 2 hours after dosing; the rate of absorption is somewhat slowed when the drug is taken with food, but the extent of absorption is not changed.

The volume of distribution of quinidine is 2 to 3 L/kg in healthy young adults, but this may be reduced to as little as 0.5 L/kg in patients with congestive heart failure, or increased to 3 to 5 L/kg in patients with cirrhosis of the liver. At concentrations of 2 to 5 mg/L (6.5 to 16.2 μmol/L), the fraction of quinidine bound to plasma proteins (mainly to α1-acid glycoprotein and to albumin) is 80 to 88% in adults and older children, but it is lower in pregnant women, and in infants and neonates it may be as low as 50 to 70%. Because α1-acid glycoprotein levels are increased in response to stress, serum levels of total quinidine may be greatly increased in settings such as acute myocardial infarction, even though the serum content of unbound (active) drug may remain normal. Protein binding is also increased in chronic renal failure, but binding abruptly descends toward or below normal when heparin is administered for hemodialysis.

Quinidine clearance typically proceeds at 3 to 5 mL/min/kg in adults, but clearance in children may be twice or three times as rapid. The elimination half-life is 6 to 8 hours in adults and 3 to 4 hours in children. Quinidine clearance is unaffected by hepatic cirrhosis, so the increased volume of distribution seen in cirrhosis leads to a proportionate increase in the elimination half-life.

Most quinidine is eliminated hepatically via the action of cytochrome P450IIIA4; there are several different hydroxylated metabolites, and some of these have antiarrhythmic activity.

The most important of quinidine’s metabolites is 3-hydroxyquinidine (3HQ), serum levels of which can exceed those of quinidine in patients receiving conventional doses of quinidine sulfate. The volume of distribution of 3HQ appears to be larger than that of quinidine, and the elimination half-life of 3HQ is about 12 hours.

As measured by antiarrhythmic effects in animals, by QTC prolongation in human volunteers, or by various in vitro techniques, 3HQ has at least half the antiarrhythmic activity of the parent compound, so it may be responsible for a substantial fraction of the effect of quinidine sulfate in chronic use.

When the urine pH is less than 7, about 20% of administered quinidine appears unchanged in the urine, but this fraction drops to as little as 5% when the urine is more alkaline. Renal clearance involves both glomerular filtration and active tubular secretion, moderated by (pH-dependent) tubular reabsorption. The net renal clearance is about 1 mL/min/kg in healthy adults. When renal function is taken into account, quinidine clearance is apparently independent of patient age.

Assays of serum quinidine levels are widely available, but the results of modern assays may not be consistent with results cited in the older medical literature. The serum levels of quinidine cited in this package insert are those derived from specific assays, using either benzene extraction or (preferably) reverse-phase high-pressure liquid chromatography. In matched samples, older assays might unpredictably have given results that were as much as two or three times higher. A typical “therapeutic” concentration range is 2 to 6 mg/L (6.2 to 18.5 μmol/L).

Mechanisms of Action

In patients with malaria, quinidine acts primarily as an intra-erythrocytic schizonticide, with little effect upon sporozites or upon pre-erythrocytic parasites. Quinidine is gametocidal to Plasmodium vivax and P. malariae, but not to P. falciparum.

In cardiac muscle and in Purkinje fibers, quinidine depresses the rapid inward depolarizing sodium current, thereby slowing phase-0 depolarization and reducing the amplitude of the action potential without affecting the resting potential. In normal Purkinje fibers, it reduces the slope of phase-4 depolarization, shifting the threshold voltage upward toward zero. The result is slowed conduction and reduced automaticity in all parts of the heart, with increase of the effective refractory period relative to the duration of the action potential in the atria, ventricles, and Purkinje tissues. Quinidine also raises the fibrillation thresholds of the atria and ventricles, and it raises the ventricular defibrillation threshold as well. Quinidine’s actions fall into class 1A in the Vaughan-Williams classification.

By slowing conduction and prolonging the effective refractory period, quinidine can interrupt or prevent reentrant arrhythmias and arrhythmias due to increased automaticity, including atrial flutter, atrial fibrillation, and paroxysmal supraventricular tachycardia. In patients with the sick sinus syndrome, quinidine can cause marked sinus node depression and bradycardia. In most patients, however, use of quinidine is associated with an increase in the sinus rate.

Quinidine prolongs the QT interval in a dose-related fashion. This may lead to increased ventricular automaticity and polymorphic ventricular tachycardias, including torsades de pointes (see WARNINGS).

In addition, quinidine has anticholinergic activity, it has negative inotropic activity, and it acts peripherally as an α-adrenergic antagonist (that is, as a vasodilator).

Clinical Effects

Maintenance of Sinus Rhythm After Conversion From Atrial Fibrillation

In six clinical trials (published between 1970 and 1984) with a total of 808 patients, quinidine (418 patients) was compared to nontreatment (258 patients) or placebo (132 patients) for the maintenance of sinus rhythm after cardioversion from chronic atrial fibrillation. Quinidine was consistently more efficacious in maintaining sinus rhythm, but a metaanalysis found that mortality in the quinidine-exposed patients (2.9%) was significantly greater than mortality in the patients who had not been treated with active drug (0.8%). Suppression of atrial fibrillation with quinidine has theoretical patient benefits (e.g., improved exercise tolerance; reduction in hospitalization for cardioversion; lack of arrhythmiarelated palpitations, dyspnea, and chest pain; reduced incidence of systemic embolism and/or stroke), but these benefits have never been demonstrated in clinical trials. Some of these benefits (e.g., reduction in stroke incidence) may be achievable by other means (anticoagulation).

By slowing the rate of atrial flutter/fibrillation, quinidine can decrease the degree of atrioventricular block and cause an increase, sometimes marked, in the rate at which supraventricular impulses are successfully conducted by the atrioventricular node, with a resultant paradoxical increase in ventricular rate (see WARNINGS).

Non-Life-Threatening Ventricular Arrhythmias

In studies of patients with a variety of ventricular arrhythmias (mainly frequent ventricular premature beats and non-sustained ventricular tachycardia), quinidine (total N=502) has been compared to flecainide (N=141), mexiletine (N=246), propafenone (N=53), and tocainide (N=67). In each of these studies, the mortality in the quinidine group was numerically greater than the mortality in the comparator group. When the studies were combined in a metaanalysis, quinidine was associated with a statistically significant threefold relative risk of death.

At therapeutic doses, quinidine’s only consistent effect upon the surface electrocardiogram is an increase in the QT interval. This prolongation can be monitored as a guide to safety, and it may provide better guidance than serum drug levels (see WARNINGS).

INDICATIONS AND USAGE

Conversion of Atrial Fibrillation/Flutter

In patients with symptomatic atrial fibrillation/flutter whose symptoms are not adequately controlled by measures that reduce the rate of ventricular response, quinidine sulfate is indicated as a means of restoring normal sinus rhythm. If this use of quinidine sulfate does not restore sinus rhythm within a reasonable time (see DOSAGE AND ADMINISTRATION), then quinidine sulfate should be discontinued.

Reduction of Frequency of Relapse Into Atrial Fibrillation/Flutter

Chronic therapy with quinidine sulfate is indicated for some patients at high risk of symptomatic atrial fibrillation/flutter, generally patients who have had previous episodes of atrial fibrillation/flutter that were so frequent and poorly tolerated as to outweigh, in the judgement of the physician and the patient, the risks of prophylactic therapy with quinidine sulfate. The increased risk of death should specifically be considered. Quinidine sulfate should be used only after alternative measures (e.g., use of other drugs to control the ventricular rate) have been found to be inadequate.

In patients with histories of frequent symptomatic episodes of atrial fibrillation/flutter, the goal of therapy should be an increase in the average time between episodes. In most patients, the tachyarrhythmia will recur during therapy, and a single recurrence should not be interpreted as therapeutic failure.

Suppression of Ventricular Arrhythmias

Quinidine sulfate is also indicated for the suppression of recurrent documented ventricular arrhythmias, such as sustained ventricular tachycardia, that in the judgement of the physician are lifethreatening. Because of the proarrhythmic effects of quinidine, its use with ventricular arrhythmias of lesser severity is generally not recommended, and treatment of patients with asymptomatic ventricular premature contractions should be avoided. Where possible, therapy should be guided by the results of programmed electrical stimulation and/or Holter monitoring with exercise.

Antiarrhythmic drugs (including quinidine sulfate) have not been shown to enhance survival in patients with ventricular arrhythmias.

Treatment of Malaria

Quinidine sulfate is also indicated in the treatment of life-threatening Plasmodium falciparum malaria.

CONTRAINDICATIONS

Quinidine is contraindicated in patients who are known to be allergic to it, or who have developed thrombocytopenic purpura during prior therapy with quinidine or quinine.

In the absence of a functioning artificial pacemaker, quinidine is also contraindicated in any patient whose cardiac rhythm is dependent upon a junctional or idioventricular pacemaker, including patients in complete atrioventricular block.

Quinidine is also contraindicated in patients who, like those with myasthenia gravis, might be adversely affected by an anticholinergic agent.

WARNINGS

Mortality

In many trials of antiarrhythmic therapy for non-life-threatening arrhythmias, active antiarrhythmic therapy has resulted in increased mortality; the risk of active therapy is probably greatest in patients with structural heart disease.

In the case of quinidine used to prevent or defer recurrence of atrial flutter/fibrillation, the best available data come from a metaanalysis CLINICAL PHARMACOLOGY/Clinical Effects above. In the patients studied in the trials there analyzed, the mortality associated with the use of quinidine was more than three times as great as the mortality associated with the use of placebo.

Another metaanalysis, also described under CLINICAL PHARMACOLOGY/Clinical Effects, showed that in patients with various non-life-threatening ventricular arrhythmias, the mortality associated with the use of quinidine was consistently greater than that associated with the use of any of a variety of alternative antiarrhythmics.

Proarrhythmic Effects

Like many other drugs (including all other class IA antiarrhythmics), quinidine prolongs the QTC interval, and this can lead to torsades de pointes, a life-threatening ventricular arrhythmia (see OVERDOSAGE). The risk of torsades is increased by bradycardia, hypokalemia, hypomagnesemia, hypocalcemia, or high serum levels of quinidine, but it may appear in the absence of any of these risk factors. The best predictor of this arrhythmia appears to be the length of the QTC interval, and quinidine should be used with extreme care in patients who have preexisting long-QT syndromes, who have histories of torsades de pointes of any cause, or who have previously responded to quinidine (or other drugs that prolong ventricular repolarization) with marked lengthening of the QTC interval. Estimation of the incidence of torsades in patients with therapeutic levels of quinidine is not possible from the available data. Other ventricular arrhythmias that have been reported with quinidine include frequent extrasystoles, ventricular tachycardia, ventricular flutter, and ventricular fibrillation.

Paradoxical Increase in Ventricular Rate in Atrial Flutter/ Fibrillation

When quinidine is administered to patients with atrial flutter/fibrillation, the desired pharmacologic reversion to sinus rhythm may (rarely) be preceded by a slowing of the atrial rate with a consequent increase in the rate of beats conducted to the ventricles. The resulting ventricular rate may be very high (greater than 200 beats per minute) and poorly tolerated. This hazard may be decreased if partial atrioventricular block is achieved prior to initiation of quinidine therapy, using conduction-reducing drugs such as digitalis, verapamil, diltiazem, or a β-receptor blocking agent.

Exacerbated Bradycardia in Sick Sinus Syndrome

In patients with the sick sinus syndrome, quinidine has been associated with marked sinus node depression and bradycardia.

Pharmacokinetic Considerations

Renal or hepatic dysfunction causes the elimination of quinidine to be slowed, while congestive heart failure causes a reduction in quinidine’s apparent volume of distribution. Any of these conditions can lead to quinidine toxicity if dosage is not appropriately reduced. In addition, interactions with coadministered drugs can alter the serum concentration and activity of quinidine, leading either to toxicity or to lack of efficacy if the dose of quinidine is not appropriately modified. (See PRECAUTIONS /Drug Interactions.)

Vagolysis

Because quinidine opposes the atrial and A-V nodal effects of vagal stimulation, physical or pharmacological vagal maneuvers undertaken to terminate paroxysmal supraventricular tachycardia may be ineffective in patients receiving quinidine.

PRECAUTIONS

Heart Block

In patients without implanted pacemakers who are at high risk of complete atrioventricular block (e.g., those with digitalis intoxication, second-degree atrioventricular block, or severe intraventricular conduction defects), quinidine should be used only with caution.

Drug Interactions

Altered Pharmacokinetics of Quinidine

Drugs that alkalinize the urine (carbonic-anhydrase inhibitors, sodium bicarbonate, thiazide diuretics) reduce renal elimination of quinidine.

By pharmacokinetic mechanisms that are not well understood, quinidine levels are increased by coadministration of amiodarone or cimetidine. Very rarely, and again by mechanisms not understood, quinidine levels are decreased by coadministration of nifedipine.

Hepatic elimination of quinidine may be accelerated by coadministration of drugs (phenobarbital, phenytoin, rifampin) that induce production of cytochrome P450IIIA4.

Perhaps because of competition for the P450IIIA4 metabolic pathway, quinidine levels rise when ketaconazole is coadministered.

Coadministration of propranolol usually does not affect quinidine pharmacokinetics, but in some studies the β-blocker appeared to cause increases in the peak serum levels of quinidine, decreases in quinidine’s volume of distribution, and decreases in total quinidine clearance. The effects (if any) of coadministration of other β-blockers on quinidine pharmacokinetics have not been adequately studied.

Diltiazem significantly decreases the clearance and increases the t1/2 of quinidine, but quinidine does not alter the kinetics of diltiazem. Hepatic clearance of quinidine is significantly reduced during coadministration of verapamil, with corresponding increases in serum levels and half-life.

Altered Pharmacokinetics of Other Drugs

Quinidine slows the elimination of digoxin and simultaneously reduces digoxin’s apparent volume of distribution. As a result, serum digoxin levels may be as much as doubled. When quinidine and digoxin are coadministered, digoxin doses usually need to be reduced. Serum levels of digoxin are also raised when quinidine is coadministered, although the effect appears to be smaller.

By a mechanism that is not understood, quinidine potentiates the anticoagulatory action of warfarin, and the anticoagulant dosage may need to be reduced. Cytochrome P450IID6 is an enzyme critical to the metabolism of many drugs, notably including mexiletine, some phenothiazines, and most polycyclic antidepressants. Constitutional deficiency of cytochrome P450IID6 is found in less than 1% of Orientals, in about 2% of American blacks, and in about 8% of American whites. Testing with debrisoquine is sometimes used to distinguish the P450IID6-deficient “poor metabolizers” from the majority-pheno-type “extensive metabolizers”.

When drugs whose metabolism is P450IID6-dependent are given to poor metabolizers, the serum levels achieved are higher, sometimes much higher, than the serum levels achieved when identical doses are given to extensive metabolizers. To obtain similar clinical benefit without toxicity, doses given to poor metabolizers may need to be greatly reduced. In the cases of prodrugs whose actions are actually mediated by P450IID6-produced metabolites (for example, codeine and hydrocodone, whose analgesic and antitussive effects appear to be mediated by morphine and hydromorphone, respectively), it may not be possible to achieve the desired clinical benefits in poor metabolizers.

Quinidine is not metabolized by cytochrome P450IID6, but therapeutic serum levels of quinidine inhibit the action of cytochrome P450IID6, effectively converting extensive metabolizers into poor metabolizers. Caution must be exercised whenever quinidine is prescribed together with drugs metabolized by cytochrome P450IID6.

Perhaps by competing for pathways of renal clearance, coadministration of quinidine causes an increase in serum levels of procainamide.

Serum levels of haloperidol are increased when quinidine is coadministered.

Presumably because both drugs are metabolized by cytochrome P450IID6, coadministration of quinidine causes variable slowing of the metabolism of nifedipine. Interactions with other dihydropyridine calcium-channel blockers have not been reported, but these agents (including felodipine, nicardipine, and nimodipine) are all dependent upon P450IIIA4 for metabolism, so similar interactions with quinidine should be anticipated.

Altered Pharmacodynamics of Other Drugs

Quinidine’s anitcholinergic, vasodilating, and negative inotropic actions may be additive to those of other drugs with these effects, and antagonistic to those of drugs with cholinergic, vasoconstricting, and positive inotropic effects. For example, when quinidine and verapamil are coadministered in doses that are each well tolerated as monotherapy, hypotension attributable to additive peripheral α-blockade is sometimes reported.

Quinidine potentiates the actions of depolarizing (succinylcholine, decamethonium) and nondepolarizing (d-tubocurarine, pancuronium) neuromuscular blocking agents. These phenomena are not well understood, but they are observed in animal models as well as in humans. In addition, in vitro addition of quinidine to the serum of pregnant women reduces the activity of pseudocholinesterase, an enzyme that is essential to the metabolism of succinylcholine.

Non-Interactions of Quinidine With Other Drugs

Quinidine has no clinically significant effect on the pharmacokinetics of diltiazem, flecainide, mephenytoin, metoprolol, propafenone, propranolol, quinine, timolol, or tocainide.

Conversely, the pharmacokinetics of quinidine are not significantly affected by caffeine, ciprofloxacin, digoxin, diltiazem, felodipine, omeprazole, or quinine. Quinidine’s pharmacokinetics are also unaffected by cigarette smoking.

Information for Patients

Before prescribing quinidine sulfate as prophylaxis against recurrence of atrial fibrillation, the physician should inform the patient of the risks and benefits to be expected (see CLINICAL PHARMACOLOGY). Discussion should include the facts:

- that the goal of therapy will be a reduction (probably not to zero) in the frequency of episodes of atrial fibrillation; and
- that reduced frequency of fibrillatory episodes may be expected, if achieved, to bring symptomatic benefit; but
- that no data are available to show that reduced frequency of fibrillatory episodes will reduce the risks of irreversible harm through stroke or death; and in fact
- that such data as are available suggest that treatment with quinidine sulfate is likely to increase the patient’s risk of death.

Carcinogenesis, Mutagenesis, Impairment of Fertility

Animal studies to evaluate quinidine’s carcinogenic or mutagenic potential have not been performed. Similarly, there are no animal data as to quinidine’s potential to impair fertility.

Pregnancy

Pregnancy Category C

Animal reproductive studies have not been conducted with quinidine. There are no adequate and well-controlled studies in pregnant women. Quinidine should be given to a pregnant woman only if clearly needed.

Human placental transport of quinidine has not been systematically studied. In one neonate whose mother had received quinidine throughout her pregnancy, the serum level of quinidine was equal to that of the mother, with no apparent ill effect. The level of quinidine in amniotic fluid was about three times higher than that found in serum. In another case, the levels of quinidine and 3-hydroxyquinidine in cord blood were about 30% of simultaneous maternal levels.

Labor and Delivery

Quinine is said to be oxytocic in humans, but there are no adequate data as to quinidine’s effects (if any) on human labor and delivery.

Nursing Mothers

Quinidine is present in human milk at levels slightly lower than those in maternal serum; a human infant ingesting such milk should (scaling directly by weight) be expected to develop serum quinidine levels at least an order of magnitude lower than those of the mother. On the other hand, the pharmacokinetics and pharmacodynamics of quinidine in human infants have not been adequately studied, and neonates’ reduced protein binding of quinidine may increase their risk of toxicity at low total serum levels. Administration of quinidine should (if possible) be avoided in lactating women who continue to nurse.

Geriatric Use

Safety and efficacy of quinidine in elderly patients has not been systematically studied.

Pediatric Use

In antimalarial trials, quinidine was as safe and effective in pediatric patients as in adults. Notwithstanding the known pharmacokinetic differences between children and adults (see CLINICAL PHARMACOLOGY, Pharmacokinetics and Metabolism), children in these trials received the same doses (on a mg/kg basis) as adults.

Safety and effectiveness of antiarrhythmic use in pediatric patients have not been established.

ADVERSE REACTIONS

Quinidine preparations have been used for many years, but there are only sparse data from which to estimate the incidence of various adverse reactions. The adverse reactions most frequently reported have consistently been gastrointestinal, including diarrhea, nausea, vomiting, and heartburn/esophagitis. In one study of 245 adult outpatients who received quinidine to suppress premature ventricular contractions, the incidences of reported adverse experiences were as shown in the table below. The most serious quinidine-associated adverse reactions are described above under WARNINGS.

Adverse Experiences in a 245-Patient PVC Trial Incidence (%)
 | Incidence (%)
diarrhea | 85 (35)
“upper gastrointestinal distress” | 55 (22)
lightheadedness | 37 (15)
headache | 18 (7)
fatigue | 17 (7)
palpitations | 16 (7)
angina-like pain | 14 (6)
weakness | 13 (5)
rash | 11 (5)
visual problems | 8 (3)
change in sleep habits | 7 (3)
tremor | 6 (2)
nervousness | 5 (2)
discoordination | 3 (1)

Vomiting and diarrhea can occur as isolated reactions to therapeutic levels of quinidine, but they may also be the first signs of cinchonism, a syndrome that may also include tinnitus, reversible high-frequency hearing loss, deafness, vertigo, blurred vision, diplopia, photophobia, headache, confusion, and delirium.

Cinchonism is most often a sign of chronic quinidine toxicity, but it may appear in sensitive patients after a single moderate dose.

A few cases of hepatotoxicity, including granulomatous hepatitis, have been reported in patients receiving quinidine. All of these have appeared during the first few weeks of therapy, and most (not all) have remitted once quinidine was withdrawn.

Autoimmune and inflammatory syndromes associated with quinidine therapy have included fever, urticaria, flushing, exfoliative rash, bronchospasm, psoriaform rash, pruritus and lymphadenopathy, hemolytic anemia, vasculitis, pneumonitis, thrombocytopenic purpura, uveitis, angioedema, agranulocytosis, the sicca syndrome, arthralgia, myalgia, elevation in serum levels of skeletal-muscle enzymes, and a disorder resembling systemic lupus erythematosus.

Convulsions, apprehension, and ataxia have been reported, but it is not clear that these were not simply the results of hypotension and consequent cerebral hypoperfusion. There are many reports of syncope. Acute psychotic reactions have been reported to follow the first dose of quinidine, but these reactions appear to be extremely rare.

Other adverse reactions occasionally reported include depression, mydriasis, disturbed color perception, night blindness, scotomata, optic neuritis, visual field loss, photosensitivity, and abnormalities of pigmentation.

To report SUSPECTED ADVERSE REACTIONS, contact Epic Pharma, LLC at 1-888-374-2791 or FDA at 1-800-FDA-1088 or www.fda.gov/medwatch

OVERDOSAGE

Overdoses with various oral formulations of quinidine have been well described. Death has been described after a 5-gram ingestion by a toddler, while an adolescent was reported to survive after ingesting 8 grams of quinidine.

The most important ill effects of acute quinidine overdoses are ventricular arrhythmias and hypotension. Other signs and symptoms of overdose may include vomiting, diarrhea, tinnitus, high-frequency hearing loss, vertigo, blurred vision, diplopia, photophobia, headache, confusion, and delirium.

Arrhythmias

Serum quinidine levels can be conveniently assayed and monitored, but the electrocardiographic QTC interval is a better predictor of quinidine-induced ventricular arrhythmias.

The necessary treatment of hemodynamically unstable polymorphic ventricular tachycardia (including torsades de pointes) is withdrawal of treatment with quinidine and either immediate cardioversion or, if a cardiac pacemaker is in place or immediately available, immediate overdrive pacing. After pacing or cardioversion, further management must be guided by the length of the QTC interval.

Quinidine-associated ventricular tachyarrhythmias with normal underlying QTC intervals have not been adequately studied. Because of the theoretical possibility of QT-prolonging effects that might be additive to those of quinidine, other antiarrhythmics with Class I (disopyramide, procainamide) or Class III activities should (if possible) be avoided.

Similarly, although the use of bretylium in quinidine overdose has not been reported, it is reasonable to expect that the α–blocking properties of bretylium might be additive to those of quinidine, resulting in problematic hypotension.

If the post-cardioversion QTC interval is prolonged, then the precardioversion polymorphic ventricular tachyarrhythmia was (by definition) torsades de pointes. In this case, lidocaine and bretylium are unlikely to be of value, and other Class I antiarrhythmics (disopyramide, procainamide) are likely to exacerbate the situation. Factors contributing to QTC prolongation (especially hypokalemia, hypomagnesemia, and hypocalcemia) should be sought out and (if possible) aggressively corrected.

Prevention of recurrent torsades may require sustained overdrive pacing or the cautious administration of isoproterenol (30 to 150 ng/kg/min).

Hypotension

Quinidine-induced hypotension that is not due to an arrhythmia is likely to be a consequence of quinidine-related α-blockade and vasorelaxation. Simple repletion of central volume Trendelenburg positioning, saline infusion) may be sufficient therapy; other interventions reported to have been beneficial in this setting are those that increase peripheral vascular resistance, including α-agonist catecholamines (norepinephrine, metaraminol) and the Military Anti-Shock Trousers.

Treatment

To obtain up-to-date information about the treatment of overdose, a good resource is your certified Regional Poison-Control Center. Telephone numbers of certified poison-control centers are listed in the Physicians’ Desk Reference (PDR). In managing overdose, consider the possibilities of multiple-drug overdoses, drug-drug interactions, and unusual drug kinetics in your patient.

Accelerated Removal

Adequate studies of orally-administered activated charcoal in human overdoses of quinidine have not been reported, but there are animal data showing significant enhancement of systemic elimination following this intervention, and there is at least one human case report in which the elimination half-life of quinidine in the serum was apparently shortened by repeated gastric lavage.

Activated charcoal should be avoided if an ileus is present; the conventional dose is 1 gram/kg, administered every 2 to 6 hours as a slurry with 8 mL/kg of tap water.

Although renal elimination of quinidine might theoretically be accelerated by maneuvers to acidify the urine, such maneuvers are potentially hazardous and of no demonstrated benefit.

Quinidine is not usually removed from the circulation by dialysis.

Following quinidine overdose, drugs that delay elimination of quinidine (cimetidine, carbonicanhydrase inhibitors, thiazide diuretics) should be withdrawn unless absolutely required.

DOSAGE AND ADMINISTRATION

Treatment of P. Falcipum Malaria

Quinidine sulfate tablets are used in one of the approved regimens for the treatment of life-threatening P. falciparum malaria. The central component of the regimen is Quinidine Gluconate Injection, and the regimen is described in the package insert of Quinidine Gluconate Injection.

Conversion of Atrial Fibrillation/Flutter to Sinus Rhythm

Especially in patients with known structural heart disease or other risk factors for toxicity, initiation or dose-adjustment of treatment with quinidine sulfate should generally be performed in a setting where facilities and personnel for monitoring and resuscitation are continuously available. Patients with symptomatic atrial fibrillation/flutter should be treated with quinidine sulfate only after ventricular rate control (e.g., with digitalis or β-blockers) has failed to provide satisfactory control of symptoms.

Adequate trials have not identified an optimal regimen of quinidine sulfate for conversion of atrial fibrillation/flutter to sinus rhythm. In one reported regimen, the patient first receives two tablets (400 mg; 332 mg of quinidine base) of quinidine sulfate every six hours. If this regimen has not resulted in conversion after 4 or 5 doses, then the dose is cautiously increased. If, at any point during administration, the QRS complex widens to 130% of its pre-treatment duration; the QTC interval widens to 130% of its pre-treatment duration and is then longer than 500 ms; P waves disappear; or the patient develops significant tachycardia, symptomatic bradycardia, or hypotension, then quinidine sulfate is discontinued, and other means of conversion (e.g., direct-current cardioversion) are considered.

Reduction of Frequency of Relapse Into Atrial Fibrillation/Flutter

In a patient with a history of frequent symptomatic episodes of atrial fibrillation/flutter, the goal of therapy with quinidine sulfate should be an increase in the average time between episodes. In most patients, the tachyarrhythmia will recur during therapy with quinidine sulfate, and a single recurrence should not be interpreted as therapeutic failure.

Especially in patients with known structural heart disease or other risk factors for toxicity, initiation or dose-adjustment of treatment with quinidine sulfate should generally be performed in a setting where facilities and personnel for monitoring and resuscitation are continuously available. Monitoring should be continued for two or three days after initiation of the regimen on which the patient will be discharged.

Therapy with quinidine sulfate should be begun with 200 mg (equivalent to 166 mg of quinidine base) every six hours. If this regimen is well tolerated, if the serum quinidine level is still well within the laboratory’s therapeutic range, and if the average time between arrhythmic episodes has not been satisfactorily increased, then the dose may be cautiously raised. The total daily dosage should be reduced if the QRS complex widens to 130% of its pretreatment duration; the QTC interval widens to 130% of its pretreatment duration and is then longer than 500 ms; P waves disappear; or the patient develops significant tachycardia, symptomatic bradycardia, or hypotension.

Suppression of Ventricular Arrhythmias

Dosing regimens for the use of quinidine sulfate in suppressing life-threatening ventricular arrhythmias have not been adequately studied. Described regimens have generally been similar to the regimen described just above for the prophylaxis of symptomatic atrial fibrillation/flutter. Where possible, therapy should be guided by the results of programmed electrical stimulation and/or Holter monitoring with exercise.

HOW SUPPLIED

Quinidine Sulfate Tablets are supplied as follows:

200 mg - White tablet scored imprinted E511

NDC 42806-513-30 bottles of 30

NDC 42806-513-01 bottles of 100

300 mg - White tablet scored imprinted E512

NDC 42806-512-30 bottles of 30

NDC 42806-512-01 bottles of 100

Store at 20° to 25°C (68° to 77°F) [see USP Controlled Room Temperature].

Dispense in a well-closed, light-resistant container.

KEEP OUT OF THE REACH OF CHILDREN.

Distributed by:

Epic Pharma, LLC

Laurelton, NY 11413

Rev.06-2023-00

MF512REV06/23

OS0005